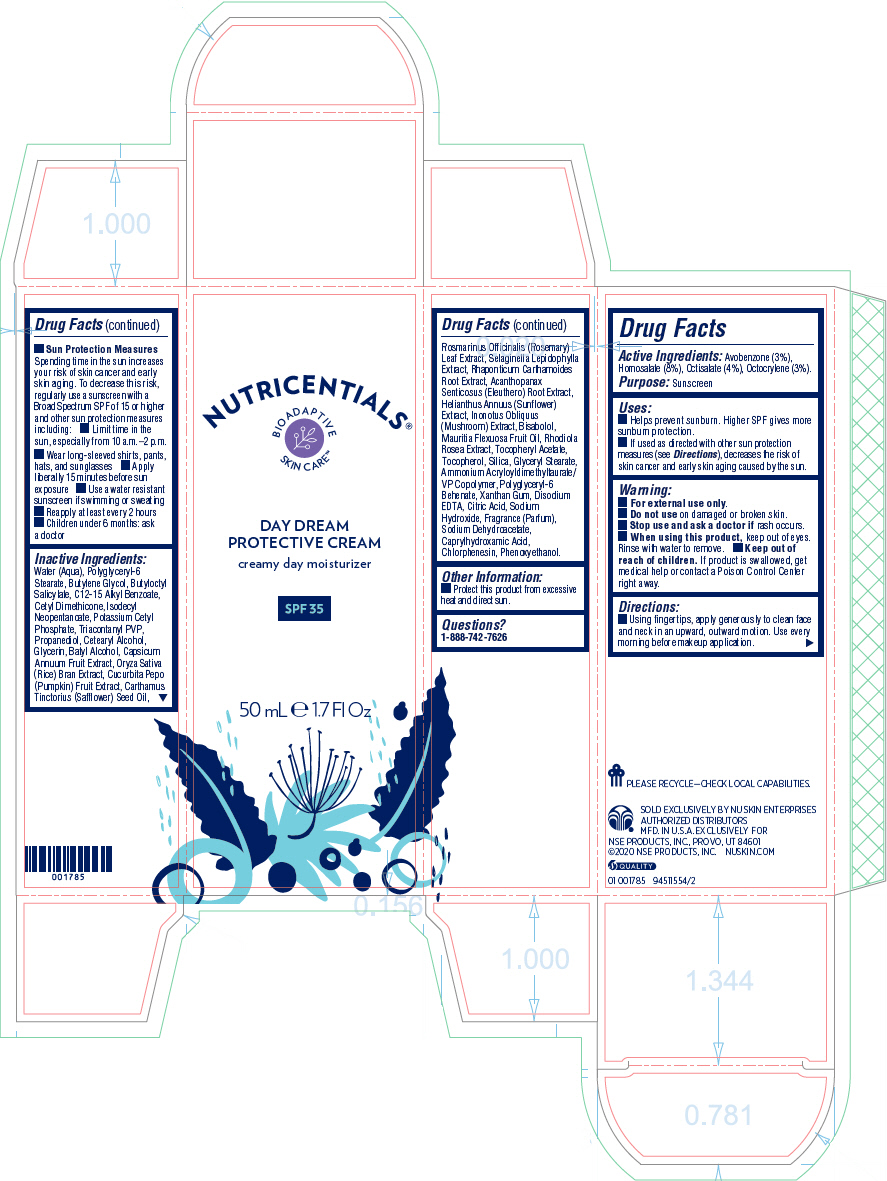 DRUG LABEL: Nutricentials Day Dream Protective
NDC: 62839-1554 | Form: CREAM
Manufacturer: NSE Products, Inc.
Category: otc | Type: HUMAN OTC DRUG LABEL
Date: 20200923

ACTIVE INGREDIENTS: Homosalate 80 mg/1 mL; Octisalate 40 mg/1 mL; Avobenzone 30 mg/1 mL; Octocrylene 30 mg/1 mL
INACTIVE INGREDIENTS: WATER; Polyglyceryl-6 Stearate; Butylene Glycol; Potassium Cetyl Phosphate; Butyloctyl Salicylate; ALKYL (C12-15) BENZOATE; Isodecyl Neopentanoate; TRICONTANYL POVIDONE; Propanediol; CETOSTEARYL ALCOHOL; Glycerin; BATILOL; PAPRIKA; SILICON DIOXIDE; GLYCERYL MONOSTEARATE; Phenoxyethanol; Ammonium Acryloyldimethyltaurate/VP Copolymer; Polyglyceryl-6 Behenate; RICE BRAN; Caprylhydroxamic Acid; Chlorphenesin; EDETATE DISODIUM ANHYDROUS; Xanthan Gum; LEVOMENOL; .ALPHA.-TOCOPHEROL ACETATE; Mauritia Flexuosa Fruit Oil; Sodium Dehydroacetate; HELIANTHUS ANNUUS FLOWERING TOP; SEDUM ROSEUM ROOT; INONOTUS OBLIQUUS FRUITING BODY; ELEUTHERO; RHAPONTICUM CARTHAMOIDES ROOT; Tocopherol; ROSEMARY; SAFFLOWER OIL; PUMPKIN; CITRIC ACID MONOHYDRATE; Sodium Hydroxide

Nutricentials® Day Dream Protective Cream

Drug Facts

Active Ingredients

Avobenzone (3%), Homosalate (8%), Octisalate (4%), Octocrylene (3%).

Purpose

Sunscreen

Uses

- Helps prevent sunburn. Higher SPF gives more sunburn protection.
- If used as directed with other sun protection measures (see Directions), decreases the risk of skin cancer and early skin aging caused by the sun.

Warning

- For external use only.

- Do not use on damaged or broken skin.

- Stop use and ask a doctor if rash occurs.

- When using this product, keep out of eyes. Rinse with water to remove.

- Keep out of reach of children. If product is swallowed, get medical help or contact a Poison Control Center right away.

Directions

- Using fingertips, apply generously to clean face and neck in an upward, outward motion. Use every morning before makeup application.
- Sun Protection Measures Spending time in the sun increases your risk of skin cancer and early skin aging. To decrease this risk, regularly use a sunscreen with a Broad Spectrum SPF of 15 or higher and other sun protection measures including:
  - Limit time in the sun, especially from 10 a.m.–2 p.m.
  - Wear long-sleeved shirts, pants, hats, and sunglasses
- Apply liberally 15 minutes before sun exposure
- Use a water resistant sunscreen if swimming or sweating
- Reapply at least every 2 hours
- Children under 6 months: ask a doctor

Inactive Ingredients

Water (Aqua), Polyglyceryl-6 Stearate, Butylene Glycol, Butyloctyl Salicylate, C12-15 Alkyl Benzoate, Cetyl Dimethicone, Isodecyl Neopentanoate, Potassium Cetyl Phosphate, Triacontanyl PVP, Propanediol, Cetearyl Alcohol, Glycerin, Batyl Alcohol, Capsicum Annuum Fruit Extract, Oryza Sativa (Rice) Bran Extract, Cucurbita Pepo (Pumpkin) Fruit Extract, Carthamus Tinctorius (Safflower) Seed Oil, Rosmarinus Officinalis (Rosemary) Leaf Extract, Selaginella Lepidophylla Extract, Rhaponticum Carthamoides Root Extract, Acanthopanax Senticosus (Eleuthero) Root Extract, Helianthus Annuus (Sunflower) Extract, Inonotus Obliquus (Mushroom) Extract, Bisabolol, Mauritia Flexuosa Fruit Oil, Rhodiola Rosea Extract, Tocopheryl Acetate, Tocopherol, Silica, Glyceryl Stearate, Ammonium Acryloyldimethyltaurate/VP Copolymer, Polyglyceryl-6 Behenate, Xanthan Gum, Disodium EDTA, Citric Acid, Sodium Hydroxide, Fragrance (Parfum), Sodium Dehydroacetate, Caprylhydroxamic Acid, Chlorphenesin, Phenoxyethanol.

Other Information

- Protect this product from excessive heat and direct sun.

Questions?

1-888-742-7626

PRINCIPAL DISPLAY PANEL - 50 mL Tube Carton

NUTRICENTIALS®
BIOADAPTIVE
SKIN CARE™

DAY DREAM
PROTECTIVE CREAM

creamy day moisturizer

SPF 35

50 mL e 1.7 Fl Oz